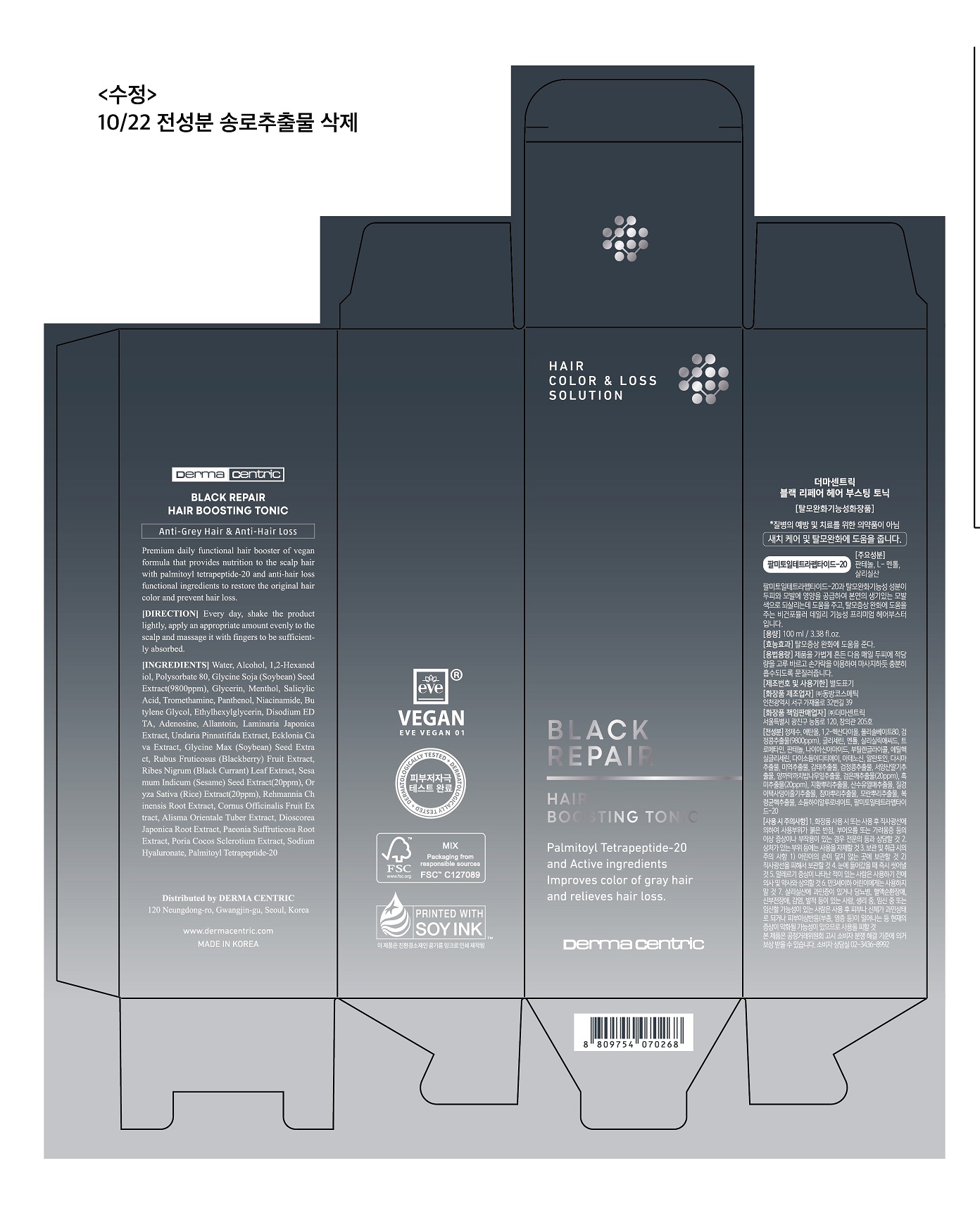 DRUG LABEL: BLACK REPAIR HAIR BOOSTING TONIC
NDC: 79593-0005 | Form: LIQUID
Manufacturer: DERMA CENTRIC INC
Category: otc | Type: HUMAN OTC DRUG LABEL
Date: 20210328

ACTIVE INGREDIENTS: SALICYLIC ACID 0.25 g/100 mL; MENTHOL 0.3 g/100 mL; DEXPANTHENOL 0.2 g/100 mL
INACTIVE INGREDIENTS: WATER; GLYCERIN

ACTIVE INGREDIENT

menthol, salicylic acid, panthenol

PURPOSE

hair care

hair loss relief

KEEP OUT OF REACH OF THE CHILDREN

WARNINGS

■ For external use only.

■ Do not use in eyes.

■ lf swallowed, get medical help promptly.

■ Stop use, ask doctor lf irritation occurs.

■ Keep out of reach of children.

DOSAGE AND ADMINISTRATION

for external use only

INACTIVE INGREDIENT

Water
Disodium EDTA
Panthenol
Allantoin
Glycerin
Niacinamide
But ylene Glycol
Sodium Hyaluronate
Adenosine
Tromethamine
Alcohol
Salicylic Acid
Ethylhexylglycer in
Menthol
Polysorbate 80
Alisma Orientale Tuber Extract
But ylene Glycol
Cornus Officinalis Fruit Extract
Dioscorea Japonica Root Extract
Ethylhexylglycer in
Paeonia Suffruticosa Root Extract
Poria Cocos Sclerotium Extract
Rehmannia Chinensis Root Extract
Glycerin
Palmitoyl Tetrapeptide-20
1,2-Hexanediol
Glycine Soja (Soybean) Seed Extract
But ylene Glycol
Ecklonia Cava Extract
Laminaria Japonica Extract
Undaria Pinnatifida Extract
Glycine Max (Soybea n) Seed Extra ct
Rubus Fruticosus (Blackberry) Fruit Extract
Ribes Nigrum (Black Currant) Leaf Extract
Sesamum Indicum (Sesame) Seed Extract
Oryza Sativa (Rice) Extract

INDICATIONS AND USAGE

shake the product lightly, apply an appropriate amount evenly to the scalp and massage it with fingers to be sufficiently absorbed